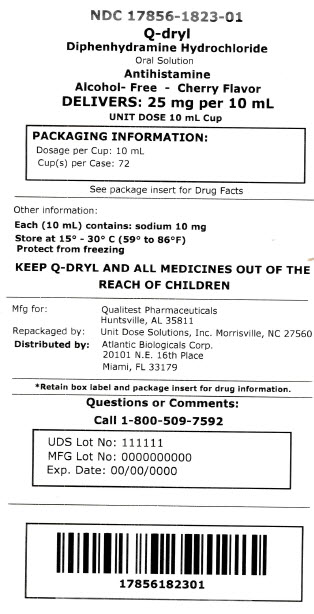 DRUG LABEL: Qdryl Allergy
NDC: 17856-1823 | Form: SOLUTION
Manufacturer: ATLANTIC BIOLOGICALS CORP
Category: otc | Type: HUMAN OTC DRUG LABEL
Date: 20161007

ACTIVE INGREDIENTS: DIPHENHYDRAMINE HYDROCHLORIDE 12.5 mg/5 mL
INACTIVE INGREDIENTS: ANHYDROUS CITRIC ACID; D&C RED NO. 33; FD&C RED NO. 40; GLYCERIN; POLOXAMER 407; POLYSORBATE 20; WATER; SACCHARIN SODIUM; SODIUM BENZOATE; SODIUM CITRATE; SUCROSE

Q-dryl Allergy

Active ingredient (in each 5 mL = 1 tsp)

Diphenhydramine HCl 12.5 mg

Purpose

Antihistamine

Uses

- temporarily relieves these symptoms due to hay fever or other upper respiratory allergies:
  - sneezing
  - runny nose
  - itchy, watery eyes
  - itching of the nose or throat

Do not use

- to make a child sleepy
- with any other product containing diphenhydramine, even one used on skin

Ask a doctor before use if you have

- glaucoma
- trouble urinating due to an enlarged prostate gland
- a breathing problem such as emphysema or chronic bronchitis

Ask a doctor or pharmacist before use if you are taking sedatives or tranquilizers.

When using this product

- marked drowsiness may occur
- avoid alcoholic drinks
- alcohol, sedatives, and tranquilizers may increase drowsiness
- be careful when driving a motor vehicle or operating machinery
- excitability may occur, especially in children

PREGNANCY OR BREAST FEEDING

If pregnant or breast-feeding, ask a health professional before use.

Keep out of reach of children.

In case of overdose, get medical help or contact a Poison Control Center right away. (1-800-222-1222)

Directions

- use an accurate measuring device to administer this medication
- take every 4 to 6 hours

children under 2 years | do not use
children 2 to 5 years | ask a doctor
children 6 years to under 12 years | 5 mL (1 tsp) to 10 mL (2 tsp); not more than 60 mL (12 tsp) in 24 hours
adults and children 12 years and over | 10 mL (2 tsp) to 20 mL (4 tsp); not more than 120 mL (24 tsp) in 24 hours

Other information

- each tsp contains: sodium 5 mg
- store at 15°- 30°C (59°- 86°F)
- protect from freezing

You may report serious side effects to: 130 Vintage Drive, Huntsville, AL 35811.

Inactive ingredients

citric acid, D&C red #33, FD&C red #40, flavor, glycerin, poloxamer 407, polysorbate 20, purified water, saccharin sodium, sodium benzoate, sodium citrate, sucrose

Made in the USAfor Qualitest Pharmaceuticals
Huntsville, AL 35811

Distributed by

Atlantic Biologicals Corp

Miami Fl 33179

Rev. 3/15 R7
8273205 0823